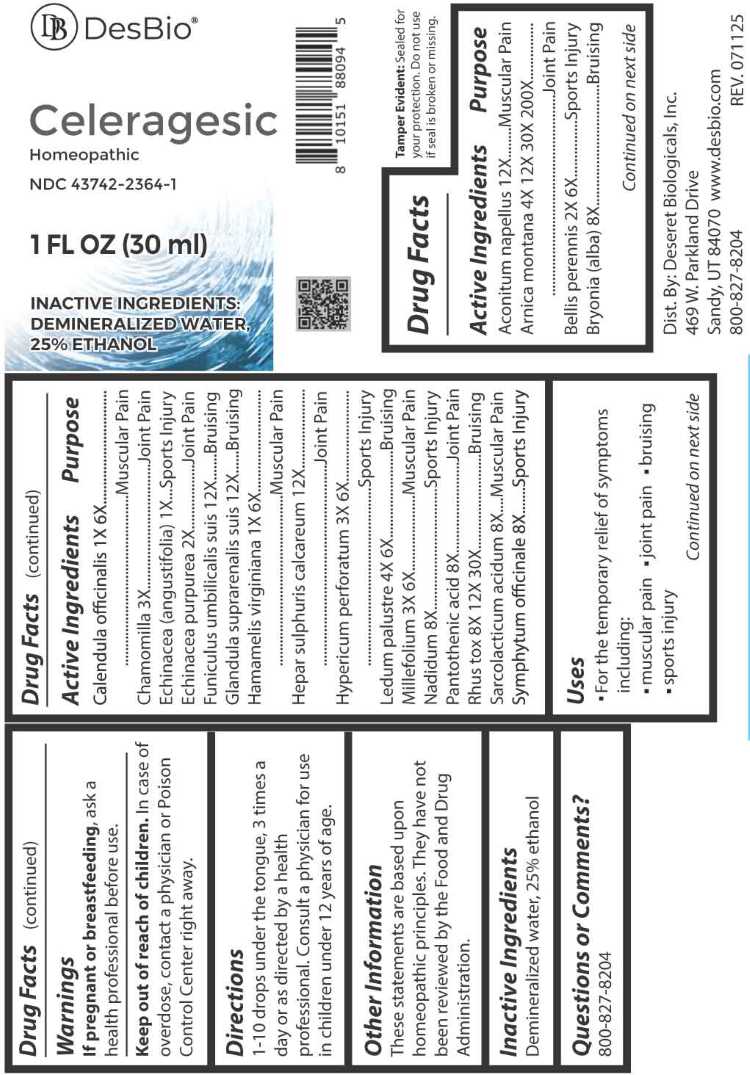 DRUG LABEL: Celeragesic
NDC: 43742-2364 | Form: LIQUID
Manufacturer: Deseret Biologicals, Inc.
Category: homeopathic | Type: HUMAN OTC DRUG LABEL
Date: 20260218

ACTIVE INGREDIENTS: ACONITUM NAPELLUS WHOLE 12 [hp_X]/1 mL; ARNICA MONTANA WHOLE 4 [hp_X]/1 mL; BELLIS PERENNIS WHOLE 2 [hp_X]/1 mL; BRYONIA ALBA ROOT 8 [hp_X]/1 mL; CALENDULA OFFICINALIS FLOWERING TOP 1 [hp_X]/1 mL; MATRICARIA CHAMOMILLA WHOLE 3 [hp_X]/1 mL; ECHINACEA ANGUSTIFOLIA WHOLE 1 [hp_X]/1 mL; ECHINACEA PURPUREA WHOLE 2 [hp_X]/1 mL; SUS SCROFA UMBILICAL CORD 12 [hp_X]/1 mL; SUS SCROFA ADRENAL GLAND 12 [hp_X]/1 mL; HAMAMELIS VIRGINIANA ROOT BARK/STEM BARK 1 [hp_X]/1 mL; CALCIUM SULFIDE 12 [hp_X]/1 mL; HYPERICUM PERFORATUM WHOLE 3 [hp_X]/1 mL; RHODODENDRON TOMENTOSUM LEAFY TWIG 4 [hp_X]/1 mL; ACHILLEA MILLEFOLIUM WHOLE 3 [hp_X]/1 mL; NADIDE 8 [hp_X]/1 mL; PANTOTHENIC ACID 8 [hp_X]/1 mL; TOXICODENDRON PUBESCENS LEAF 8 [hp_X]/1 mL; LACTIC ACID, L- 8 [hp_X]/1 mL; COMFREY ROOT 8 [hp_X]/1 mL
INACTIVE INGREDIENTS: WATER; ALCOHOL

DRUG FACTS:

ACTIVE INGREDIENT:

Aconitum Napellus 12X, Arnica Montana 4X, 12X, 30X, 200X, Bellis Perennis 2X, 6X, Bryonia (Alba) 8X, Calendula Officinalis 1X, 6X, Chamomilla 3X, Echinacea (Angustifolia) 1X, Echinacea Purpurea 2X, Funiculus Umbilicalis Suis 12X, Glandula Suprarenalis Suis 12X, Hamamelis Virginiana 1X, 6X, Hepar Sulphuris Calcareum 12X, Hypericum Perforatum 3X, 6X, Ledum Palustre 4X, 6X, Millefolium 3X, 6X, Nadidum 8X, Pantothenic Acid 8X, Rhus Tox 8X, 12X, 30X, Sarcolacticum Acidum 8X, Symphytum Officinale 8X.

PURPOSE:

Aconitum Napellus – Muscular Pain, Arnica Montana – Joint Pain, Bellis Perennis – Sports Injury, Bryonia (Alba) - Bruising, Calendula Officinalis – Muscular Pain, Chamomilla – Joint Pain, Echinacea (Angustifolia) – Sports Injury, Echinacea Purpurea – Joint Pain, Funiculus Umbilicalis Suis - Bruising, Glandula Suprarenalis Suis - Bruising, Hamamelis Virginiana – Muscular Pain, Hepar Sulphuris Calcareum – Joint Pain, Hypericum Perforatum – Sports Injury, Ledum Palustre - Bruising, Millefolium – Muscular Pain, Nadidum – Sports Injury, Pantothenic Acid – Join Pain, Rhus Tox - Bruising, Sarcolacticum Acidum – Muscular Pain, Symphytum Officinale – Sports Injury

USES:

• For the temporary relief of symptoms including:

• muscular pain • joint pain • bruising • sports injury

These statements are based upon homeopathic principles. They have not been reviewed by the Food and Drug Administration.

WARNINGS:

If pregnant or breastfeeding, ask a health professional before use.

Keep out of reach of children. In case of overdose, contact a physician or Poison Control Center right away.

Tamper Evident: Sealed for your protection. Do not use if seal is broken or missing.

KEEP OUT OF REACH OF CHILDREN:

In case of overdose, contact physician or a Poison Control Center right away.

DIRECTIONS:

1-10 drops under the tongue, 3 times a day or as directed by a health professional.
Consult a physician for use in children under 12 years of age.

INACTIVE INGREDIENTS:

Demineralized water, 25% ethanol

QUESTIONS:

Dist. By: Deseret Biologicals, Inc.

469 W. Parkland Drive

Sandy, UT 84070

www.desbio.com

800-827-8204

PACKAGE LABEL DISPLAY:

DesBio

Celeragesic

Homeopathic

NDC 43742-2364-1

1 FL OZ (30 ml)